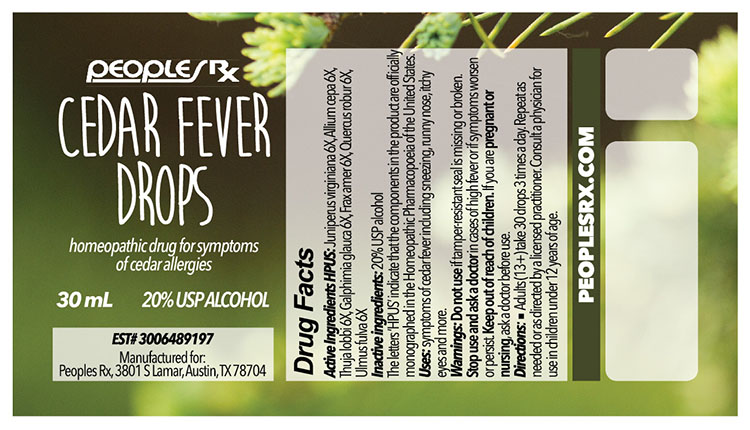 DRUG LABEL: Cedar Fever
NDC: 69406-002 | Form: LIQUID
Manufacturer: People's Pharmacy, Inc
Category: homeopathic | Type: HUMAN OTC DRUG LABEL
Date: 20160127

ACTIVE INGREDIENTS: ONION 6 [hp_X]/30 mL; FRAXINUS AMERICANA BARK 6 [hp_X]/30 mL; GALPHIMIA GLAUCA FLOWERING TOP 6 [hp_X]/30 mL; JUNIPERUS VIRGINIANA TWIG 6 [hp_X]/30 mL; QUERCUS ROBUR TWIG BARK 6 [hp_X]/30 mL; THUJA PLICATA LEAF 6 [hp_X]/30 mL; ULMUS RUBRA BARK 6 [hp_X]/30 mL
INACTIVE INGREDIENTS: ALCOHOL

DRUG FACTS

ACTIVE INGREDIENTS

JUNIPERUS VIRGINIANA 6X

ALLIUM CEPA 6X

THUJA LOBBI 6X

GALPHIMIA GLAUCA 6X

FRAX AMER 6X

QUERCUS ROBUR 6X

ULMUS FULVA 6X

USES

To relieve the symptoms of cedar allergies including sneezing, runny nose, itching eyes and more.

Keep out of reach of children. If you are pregnant or nursing, ask a doctor before use.

INDICATIONS

JUNIPERUS VIRGINIANA Allergies

ALLIUM CEPA Head cold

THUJA LOBBI Dry, hacking cough

GALPHIMIA GLAUCA Sneezing

FRAX AMER Fever sores on lips

QUERCUS ROBUR Diarrhea

ULMUS FULVA Constipation

WARNINGS

Do not use if tamper-resistant seal is missing or broken. Stop use and ask a doctor in cases of high fever or if symptoms persist.

DIRECTIONS

Adults (13+) take 30 drops 3 times a day. Repeat as needed or as instructed by a licensed practitioner. Consult a physician for use in children under 12 years of age.

INACTIVE INGREDIENTS

20% USP alcohol